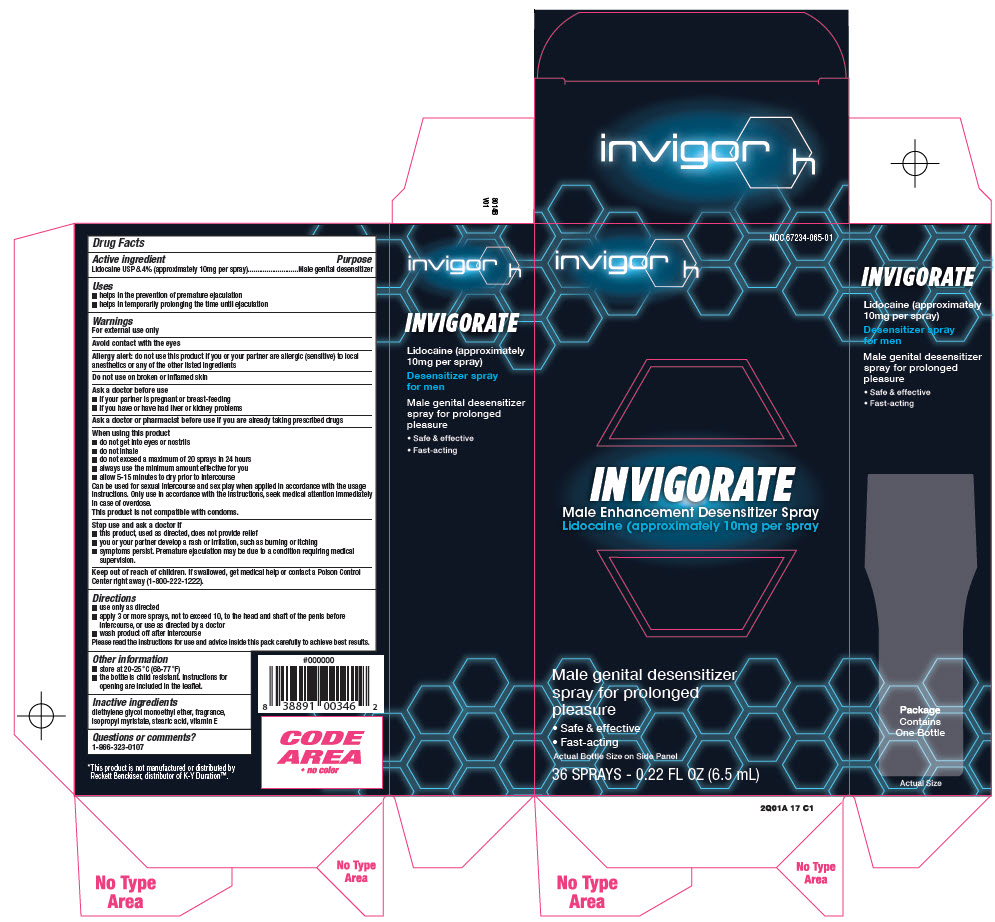 DRUG LABEL: INVIGOR OH
NDC: 67234-065 | Form: SPRAY
Manufacturer: Natureplex LLC
Category: otc | Type: HUMAN OTC DRUG LABEL
Date: 20250710

ACTIVE INGREDIENTS: Lidocaine 8.4 g/100 mL
INACTIVE INGREDIENTS: Diethylene Glycol Monoethyl Ether; Coumarin; Isopropyl Myristate; Stearic Acid; .Alpha.-Tocopherol

INVIGOR OH

Drug Facts

Active ingredient

Lidocaine USP 8.4% (approximately 10mg per spray)

Purpose

Male genital desensitizer

Uses

- helps in the prevention of premature ejaculation
- helps in temporarily prolonging the time until ejaculation

Warnings

For external use only

Avoid contact with the eyes

Allergy alert: do not use this product if you or your partner are allergic (sensitive) to local anesthetics or any of the other listed ingredients

Do not use on broken or inﬂamed skin

Ask a doctor before use

- if your partner is pregnant or breast-feeding
- if you have or have had liver or kidney problems

Ask a doctor or pharmacist before use if you are already taking prescribed drugs

When using this product

- do not get into eyes or nostrils
- do not inhale
- do not exceed a maximum of 20 sprays in 24 hours
- always use the minimum amount effective for you
- allow 5-15 minutes to dry prior to intercourse

Can be used for sexual intercourse and sex play when applied in accordance with the usage instructions. Only use in accordance with the instructions, seek medical attention immediately in case of overdose.

This product is not compatible with condoms.

Stop use and ask a doctor if

- this product, used as directed, does not provide relief
- you or your partner develop a rash or irritation, such as burning or itching
- symptoms persist. Premature ejaculation may be due to a condition requiring medical supervision.

Keep out of reach of children. If swallowed, get medical help or contact a Poison Control Center right away (1-800-222-1222).

Directions

- use only as directed
- apply 3 or more sprays, not to exceed 10, to the head and shaft of the penis before intercourse, or use as directed by a doctor
- wash product off after intercourse

Please read the instructions for use and advice inside this pack carefully to achieve best results.

Other information

- store at 20-25° C (68-77 °F)
- the bottle is child resistant. Instructions for opening are included in the leaﬂet.

Inactive ingredients

diethylene glycol monoethyl ether, fragrance, isopropyl myristate, stearic acid, vitamin E

Questions or comments?

1-866-323-0107

PRINCIPAL DISPLAY PANEL - 6.5 mL Bottle Carton

NDC 67234-065-01

invigor h

INVIGORATE
Male Enhancement Desensitizer Spray
Lidocaine (approximately 10mg per spray

Male genital desensitizer
spray for prolonged
pleasure

• Safe & effective
• Fast-acting

Actual Bottle Size on Side Panel

36 SPRAYS - 0.22 FL OZ (6.5 mL)